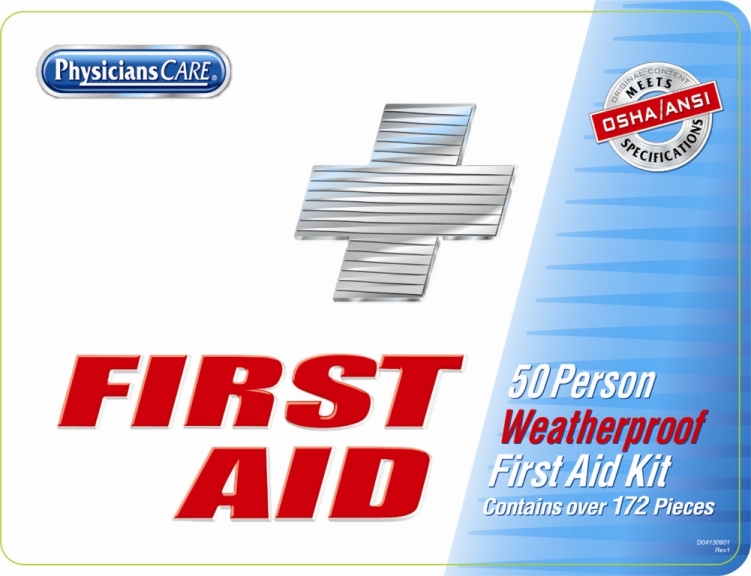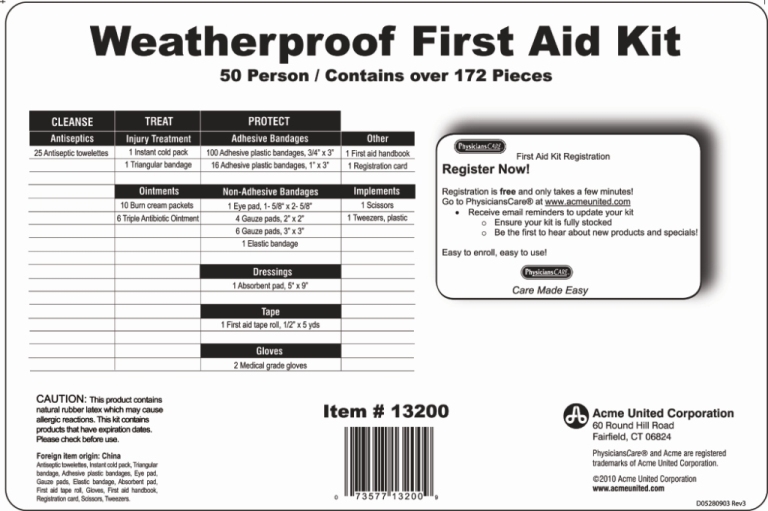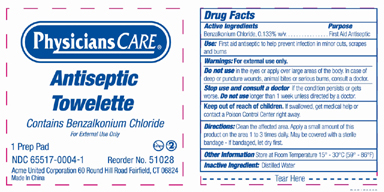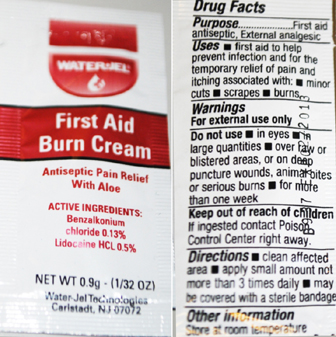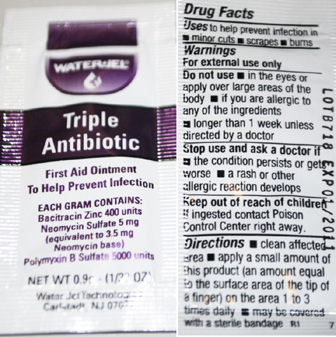 DRUG LABEL: Weatherproof First Aid Kit
NDC: 65517-0017 | Form: KIT | Route: TOPICAL
Manufacturer: Dukal Corporation
Category: other | Type: MEDICAL DEVICE
Date: 20100910

ACTIVE INGREDIENTS: BENZALKONIUM CHLORIDE 0.00186 mL/1.4 mL; BACITRACIN ZINC 400 [iU]/1 g; NEOMYCIN SULFATE 3.5 mg/1 g; POLYMYXIN B SULFATE 5000 [iU]/1 g; BENZALKONIUM CHLORIDE 0.13 g/100 g; LIDOCAINE HYDROCHLORIDE 0.5 g/100 g
INACTIVE INGREDIENTS: WATER 1.39814 mL/1.4 mL; PETROLATUM; EDETATE DISODIUM; LIGHT MINERAL OIL; STEARIC ACID; POLYETHYLENE GLYCOL; CETYL ALCOHOL; TROLAMINE; GLYCERIN; METHYLPARABEN; PROPYLENE GLYCOL; DIAZOLIDINYL UREA; ALOE VERA LEAF; WATER; PROPYLPARABEN; GLYCERYL MONOSTEARATE

Content Card

HOW SUPPLIED

Weatherproof First Aid Kit

50 Person / Contains over 172 pieces

CLEANSE

Antiseptics

25 Antiseptic Towelettes

TREAT

Injury Treatment

1 Instant cold pack
1 Triangular Bandage

Ointments

10 Burn cream packets
6 Triple Antibiotic Ointment

PROTECT

Adhesive Bandages

100 Adhesive plastic bandages, 3/4” x 3”
16 Adhesive plastic bandages, 1" x 3"

Non-Adhesive Bandages

1 Eye Pad 1 - 5/8" x 2 - 5/8"
4 Gauze pads 2" x 2"
6 Gauze pads 3" x 3'
1 Elastic bandage

Dressings

1 Absorbent pad 5" x 9"
Tape
1 First aid tape roll, 1/2” x 5 yds
Gloves
2 Medical grade gloves
Other
1 First aid handbook
1 Registration card
Implements
1 Scissors
1 Tweezers, plastic

GENERAL PRECAUTIONS

CAUTION: This product contains
natural rubber latex which may cause
allergic reactions. This kit contains
products that have expiration dates.
Please check before use.

REFERENCES

Foreign item origin: China
Antiseptic towelettes, Instant cold pack, Triangular
Bandage, Adhesive plastic bandages, Eye Pad,
Gauze pads, Elastic bandage, Absorbent pad,
First aid tape roll, Gloves, First aid handbook,
Registration card, Scissors,Tweezers.

PACKAGE LABEL

Acme United Corporation
60 Round Hill Road
Fairfield, CT 06824

PhysiciansCare® and Acme are registered
trademarks of Acme United Corporation.

©2010 Acme United Corporation
www.acmeunited.com

Antiseptic Towelette Labeling

Reorder 51028

NDC 65517-0004-1

Physicians Care

Antiseptic Towelette

Contains Benzalkonium Chloride

For External Use Only

1 Prep Pad

Acme United Corporation, 60 Round Hill Road, Fairfield, CT 06824

Made in China

Drug Facts

Active Ingredients..................... Benzalkonium Chloride

Purpose................................. First Aid Antiseptic

Use First aid antiseptic to help prevent infection in minor cuts, scrapes and burns

Warnings

- For External Use Only

Do Not Use

- in the eyes or apply over large areas of the body. In case
  of deep or puncture wounds, animal bites or serious burns, consult a doctor.

Stop Use and consult a doctor

If the condition persists or gets worse.

Do not use longer than 1 week unless directed by a doctor.

Keep out of reach of children. If swallowed get medical help or

contact a Poison Control Center right away.

Directions

Clean the affected area. Apply a small amount of this product

on the area 1 to 3 times daily. May be covered with a sterile

bandage - if bandaged, let dry first.

Other Information

Store at Room Temperature 15 - 30 C (59 - 86 F)

Inactive Ingredient purified water

Triple Antibiotic Labeling

WaterJel

Triple Antibiotic

First Aid Ointment

To Help Prevent Infection

Each Gram contains

Bacitracin Zinc 400 units

Neomycin Sulphate 5 mg

(equivalent to 3.5 mg Neomycin base)

Polymyxin B Sulfate 5000 units

Water-Jel Technologies

Carlstadt, NJ 07072

Drug Facts

Uses to help prevent infection in

minor cuts, scrapes, burns

Warnings

For external use only

Do not use

in the eyes or apply over large areas of the body

If you are allergic to any of the ingredients

longer than 1 week unless directed by a doctor

Stop use and ask a doctor if

the condition persists or gets worse

a rash or other allergic reaction develops

Keep out of reach of children

if ingested contact Poison Control Center right away

Directions

clean affected area apply a small amount of product

(an amount equal to the surface area of the tip of a finger)

on the area 1 to 3 times daily may be covered with a sterile bandage

First Aid Burn Cream Labeling

WaterJel

First Aid Burn Cream

Antiseptic Pain Relief with Aloe

Active Ingredients:

Benzalkonium Chloride 0.13%

Lidocaine HCL 0.5%

Water-Jel Technologies

Carlstadt, NJ 07072

Drug Facts

Purpose

First Aid Antiseptic, External analgesic

Uses

first aid to help prevent infection and for temporary

relief of pain an itching associated with minor cuts,

scrapes, burns

Warnings

For external use only

Do not use

in the eyes

in large quantities over raw or blistered areas or on

deep puncture wounds, animal bites, or serious burns

Keep out of reach of children

if ingested contact Poison Control Center right away

Directions

clean affected area apply a small amount not more

than 3 times daily may be covered with a sterile bandage

Other Information

Store at room temperature